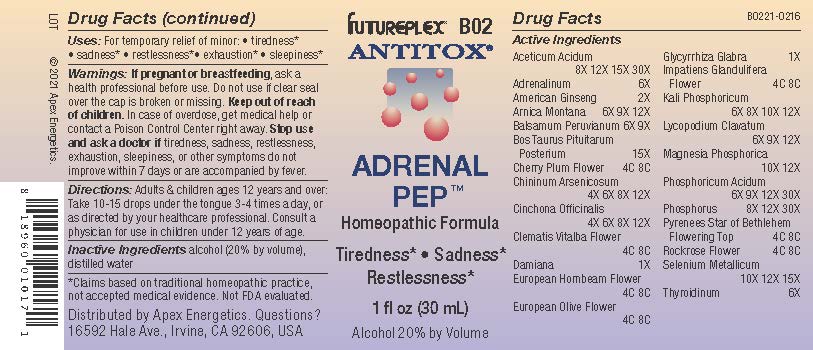 DRUG LABEL: B02
NDC: 63479-0202 | Form: SOLUTION/ DROPS
Manufacturer: Apex Energetics Inc.
Category: homeopathic | Type: HUMAN OTC DRUG LABEL
Date: 20240108

ACTIVE INGREDIENTS: DIBASIC POTASSIUM PHOSPHATE 12 [hp_X]/1 mL; EPINEPHRINE 6 [hp_X]/1 mL; LYCOPODIUM CLAVATUM SPORE 12 [hp_X]/1 mL; PHOSPHORIC ACID 30 [hp_X]/1 mL; TURNERA DIFFUSA LEAFY TWIG 1 [hp_X]/1 mL; BALSAM PERU 9 [hp_X]/1 mL; QUININE ARSENITE 12 [hp_X]/1 mL; CLEMATIS VITALBA FLOWER 8 [hp_C]/1 mL; CARPINUS BETULUS FLOWER 8 [hp_C]/1 mL; GLYCYRRHIZA GLABRA 1 [hp_X]/1 mL; IMPATIENS GLANDULIFERA FLOWER 8 [hp_C]/1 mL; HELIANTHEMUM NUMMULARIUM FLOWER 8 [hp_C]/1 mL; SELENIUM 15 [hp_X]/1 mL; MAGNESIUM PHOSPHATE, DIBASIC TRIHYDRATE 12 [hp_X]/1 mL; ORNITHOGALUM UMBELLATUM FLOWERING TOP 8 [hp_C]/1 mL; THYROID, UNSPECIFIED 6 [hp_X]/1 mL; PHOSPHORUS 30 [hp_X]/1 mL; BOS TAURUS PITUITARY GLAND, POSTERIOR 15 [hp_X]/1 mL; OLEA EUROPAEA FLOWER 8 [hp_C]/1 mL; PRUNUS CERASIFERA FLOWER 8 [hp_C]/1 mL; CINCHONA OFFICINALIS BARK 12 [hp_X]/1 mL; ACETIC ACID 30 [hp_X]/1 mL; AMERICAN GINSENG 2 [hp_X]/1 mL; ARNICA MONTANA 12 [hp_X]/1 mL
INACTIVE INGREDIENTS: WATER; ALCOHOL

B02

Active Ingredients
ACETICUM ACIDUM | 8X 12X 15X 30X
ADRENALINUM | 6X
AMERICAN GINSENG | 2X
ARNICA MONTANA | 6X 9X 12X
BALSAMUM PERUVIANUM | 6X 9X
BOS TAURUS PITUITARUM POSTERIUM | 15X
CHERRY PLUM FLOWER | 4C 8C
CHININUM ARSENICOSUM | 4X 6X 8X 12X
CINCHONA OFFICINALIS | 4X 6X 8X 12X
CLEMATIS VITALBA FLOWER | 4C 8C
DAMIANA | 1X
EUROPEAN HORNBEAM FLOWER | 4C 8C
EUROPEAN OLIVE FLOWER | 4C 8C
GLYCYRRHIZA GLABRA | 1X
IMPATIENS GLANDULIFERA FLOWER | 4C 8C
KALI PHOSPHORICUM | 6X 8X 10X 12X
LYCOPODIUM CLAVATUM | 6X 9X 12X
MAGNESIA PHOSPHORICA | 10X 12X
PHOSPHORICUM ACIDUM | 6X 9X 12X 30X
PHOSPHORUS | 8X 12X 30X
PYRENEES STAR OF BETHLEHEM FLOWERING TOP | 4C 8C
ROCKROSE FLOWER | 4C 8C
SELENIUM METALLICUM | 10X 12X 15X
THYROIDINUM | 6X

INDICATIONS AND USAGE

Uses:

For temporary relief of minor:

tiredness*

sadness*

restlessness*

exhaustion*

sleepiness*

*Claims based on traditional homeopathic practice, not accepted medical evidence. Not FDA evaluated.

Warnings:

PREGNANCY OR BREAST FEEDING

If pregnant or breastfeeding, ask a health professional before use.

Do not use if clear seal over the cap is broken or missing.

Keep out of reach of children. In case of overdose, get medical help or contact a Poison Control Center right away.

Stop use and ask a doctor if tiredness, sadness, restlessness, exhaustion, sleepiness, or other symptoms do not improve within 7 days or are accompanied by fever.

DOSAGE AND ADMINISTRATION

Adults & children ages 12 years and over: Take 10-15 drops under the tongue 3-4 times a day, or as directed by your healthcare professional. Consult a physician for use in children under 12 years of age.

INACTIVE INGREDIENT

alcohol (20% by volume), distilled water

Distributed by Apex Energetics. Questions?

16592 Hale Ave., Irvine, CA 92606, USA

PACKAGE LABEL

FUTUREPLEX® B02

ANTITOX®

ADRENAL PEP™

Homeopathic Formula

Tiredness*

Sadness*

Restlessness*

1 fl oz (30 mL)

Alcohol 20% by Volume